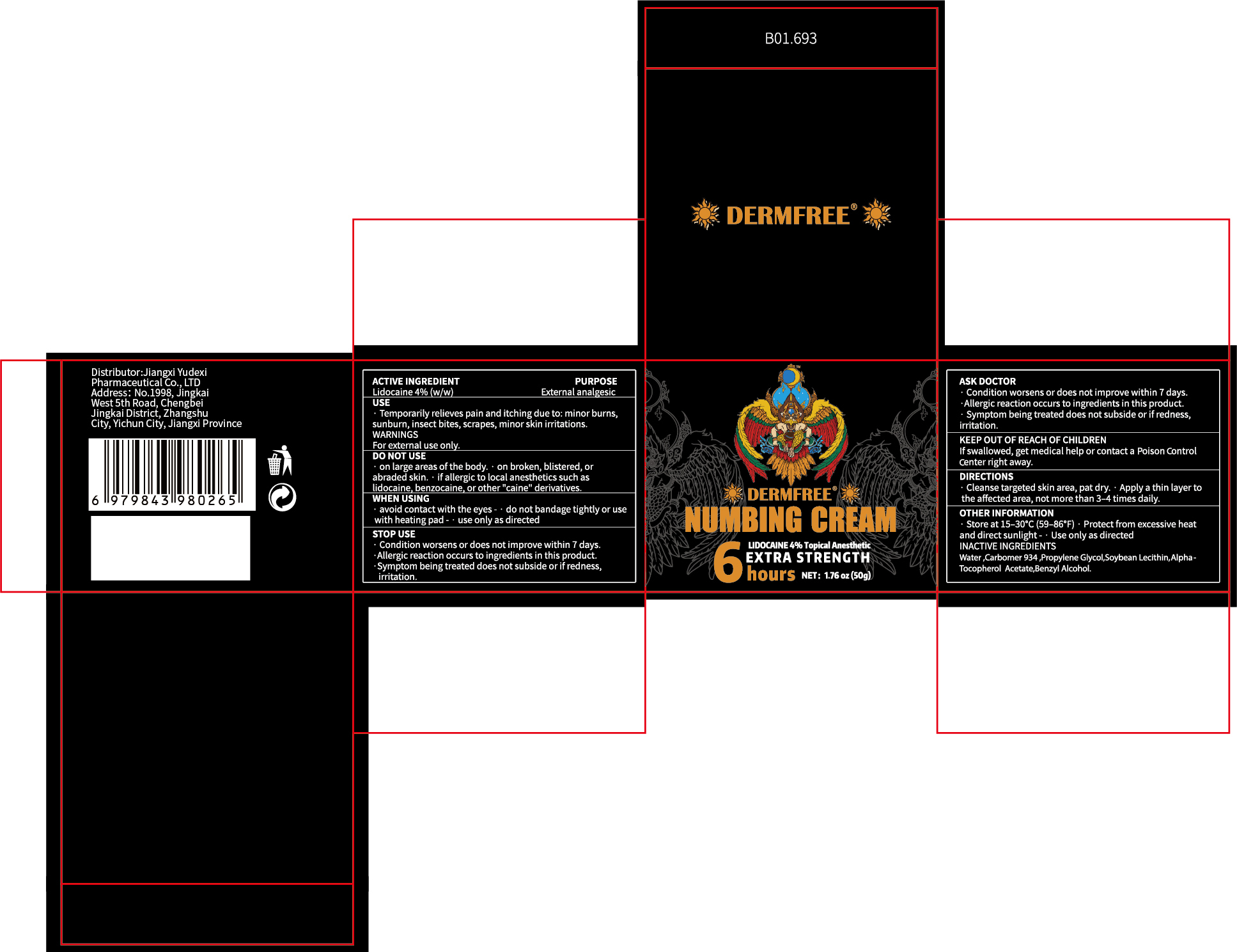 DRUG LABEL: DERMFREE  NUMBING
NDC: 85248-121 | Form: CREAM
Manufacturer: Jiangxi Yudexi Pharmaceutical Co., LTD
Category: otc | Type: HUMAN OTC DRUG LABEL
Date: 20260208

ACTIVE INGREDIENTS: LIDOCAINE 4 g/100 g
INACTIVE INGREDIENTS: WATER; SOYBEAN LECITHIN; .ALPHA.-TOCOPHEROL ACETATE; BENZYL ALCOHOL; CARBOMER 934; PROPYLENE GLYCOL

85248-121

Active Ingredient

Lidocaine 4%(W/W)

Purpose

External analgesic

Use

·Temporarily relieves pain and itching due to: minor burns,sunburn, insect bites, scrapes, minor skin irritations

Warnings

For external use only.

Do not use

·on large areas of the body.·on broken, blistered, or abraded skin. · if allergic to local anesthetics such as lidocaine, benzocaine, or other "caine" derivatives

When Using

·avoid contact with the eyes - ·do not bandage tightly or use with heating pad -· use only as directed

Stop Use

·Condition worsens or does not improve within 7 days.·Allergic reaction occurs to ingredients in this product.·Symptom being treated does not subside or if redness,irritation

Ask Doctor

·Condition worsens or does not improve within 7 days.·Allergic reaction occurs to ingredients in this product.·Symptom being treated does not subside or if redness,irritation

Keep Oot Of Reach Of Children

lf swallowed, get medical help or contact a Poison Control Center right away.

Directions

·Cleanse targeted skin area, pat dry. ·Apply a thin layer to the affected area, not more than 3-4 times daily.

Other information

Store at 15-30°C(59-86°F)·Protect from excessive heat and direct sunlight-· Use only as directed

Inactive ingredients

Water,Carbomer934, propylene Glycol,Soybean Lecithin,Alpha-Tocopherol Acetate,Benzyl Alcohol.